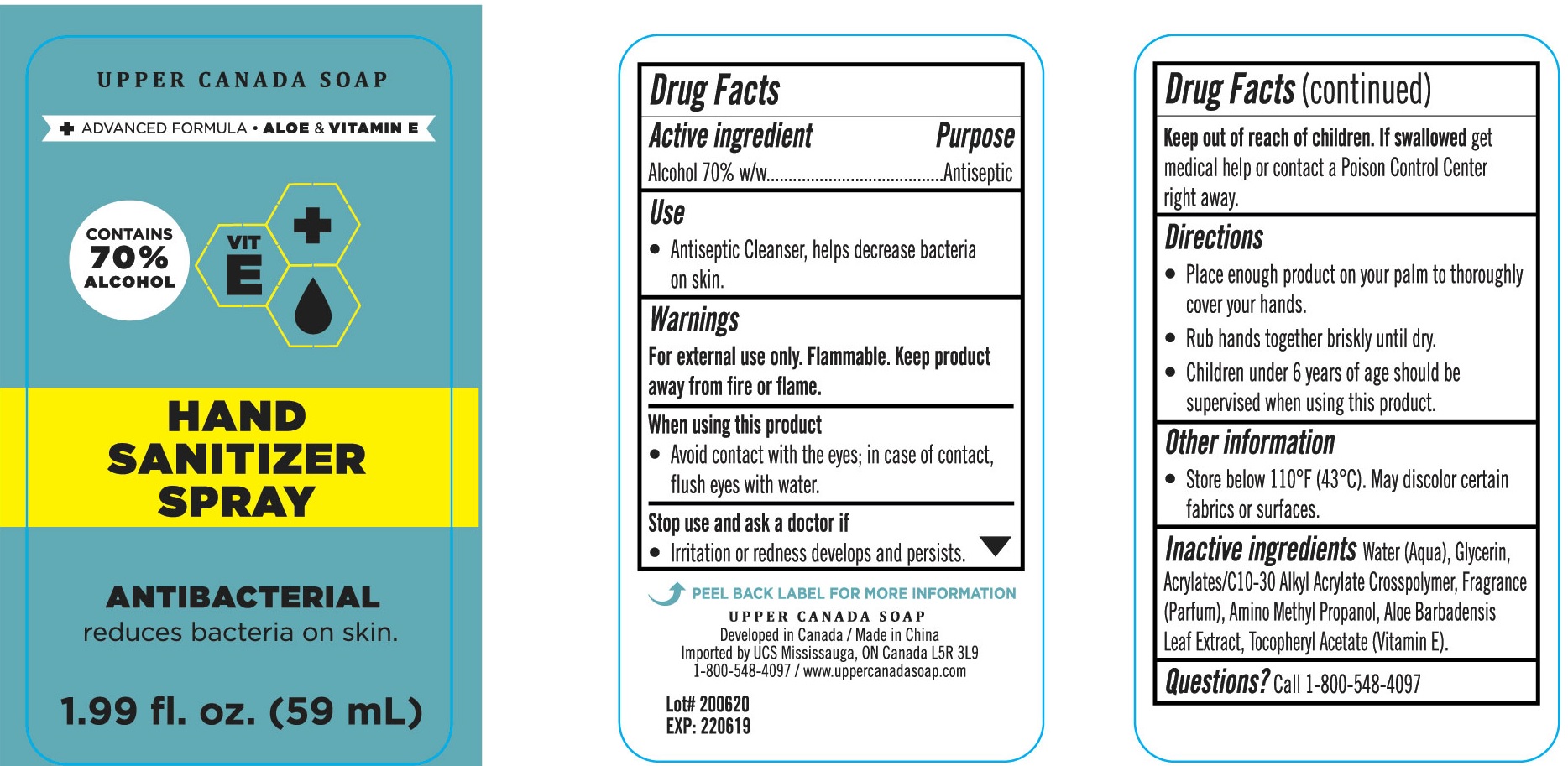 DRUG LABEL: Bye Bye Germs HAND SANITIZER
NDC: 56136-311 | Form: LIQUID
Manufacturer: Ganzhou Olivee Cosmetic Co., Ltd.
Category: otc | Type: HUMAN OTC DRUG LABEL
Date: 20200930

ACTIVE INGREDIENTS: ALCOHOL 70 mL/100 mL
INACTIVE INGREDIENTS: WATER; CARBOMER INTERPOLYMER TYPE A (ALLYL SUCROSE CROSSLINKED); AMINOMETHYLPROPANOL; CARBOMER COPOLYMER TYPE A; .ALPHA.-TOCOPHEROL ACETATE, DL-; ALOE VERA LEAF

BYE BYE GERMS HAND SANITIZER

Active ingredient

Alcohol 70% w/w

Purpose

Antiseptic Cleanser.

Use

Antiseptic Cleanser, Help decrease bacteria on skin.

Warnings

For external use only.

Flammable. Keep product away from fire or flame.

When using this product

avoid contact with eyes; in case of contact, flush eyes with water.

Stop use and ask a doctor if

irritation or redness develops and persists.

Keep out of reach of children.

If swallowed, get medical help or contact a Poison Control Center right away.

Directions

Place enough product on your palm to thoroughly cover your hads. Rub hands together briskly until dry. Children under 6 years of age should be supervised when using this product.

Inactive ingredients

Water (Aqua), Acrylates/C10-30 Alkyl Acrylate Crosspolymer, Aminomethyl Propanol, Glycerin, Fragrance (Parfum), Aloe Barbadensis Leaf Extract, Tocopheryl Actate (Vitamin E)

Other information:

Store below 110℉ （43℃）. May discolor certain fabrics or surfaces.